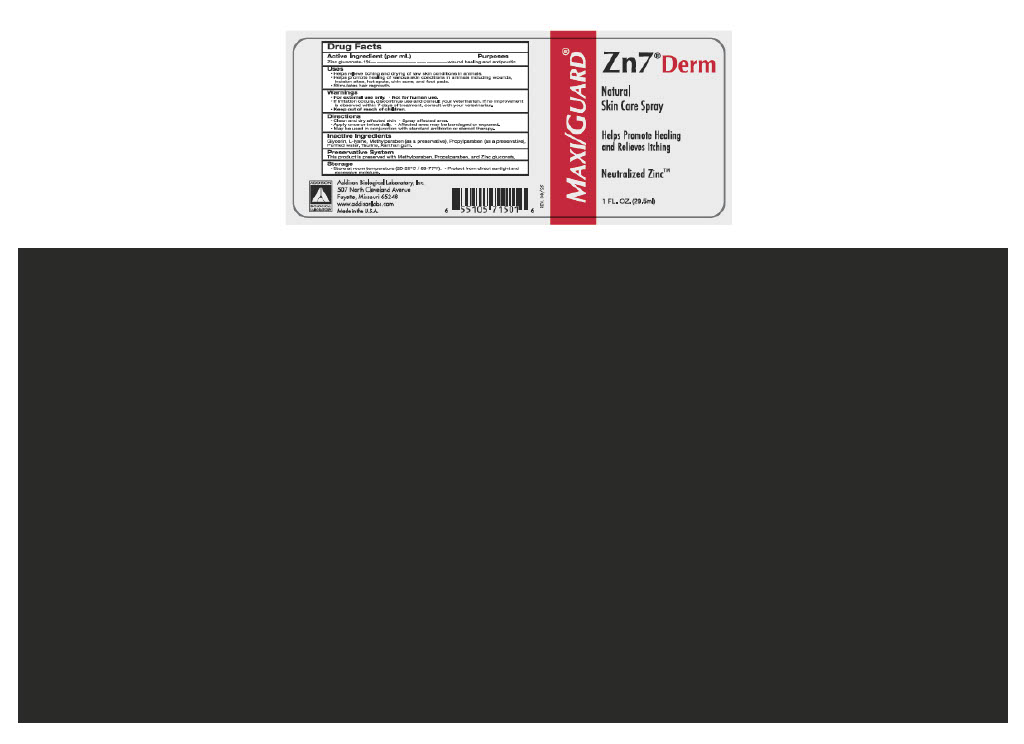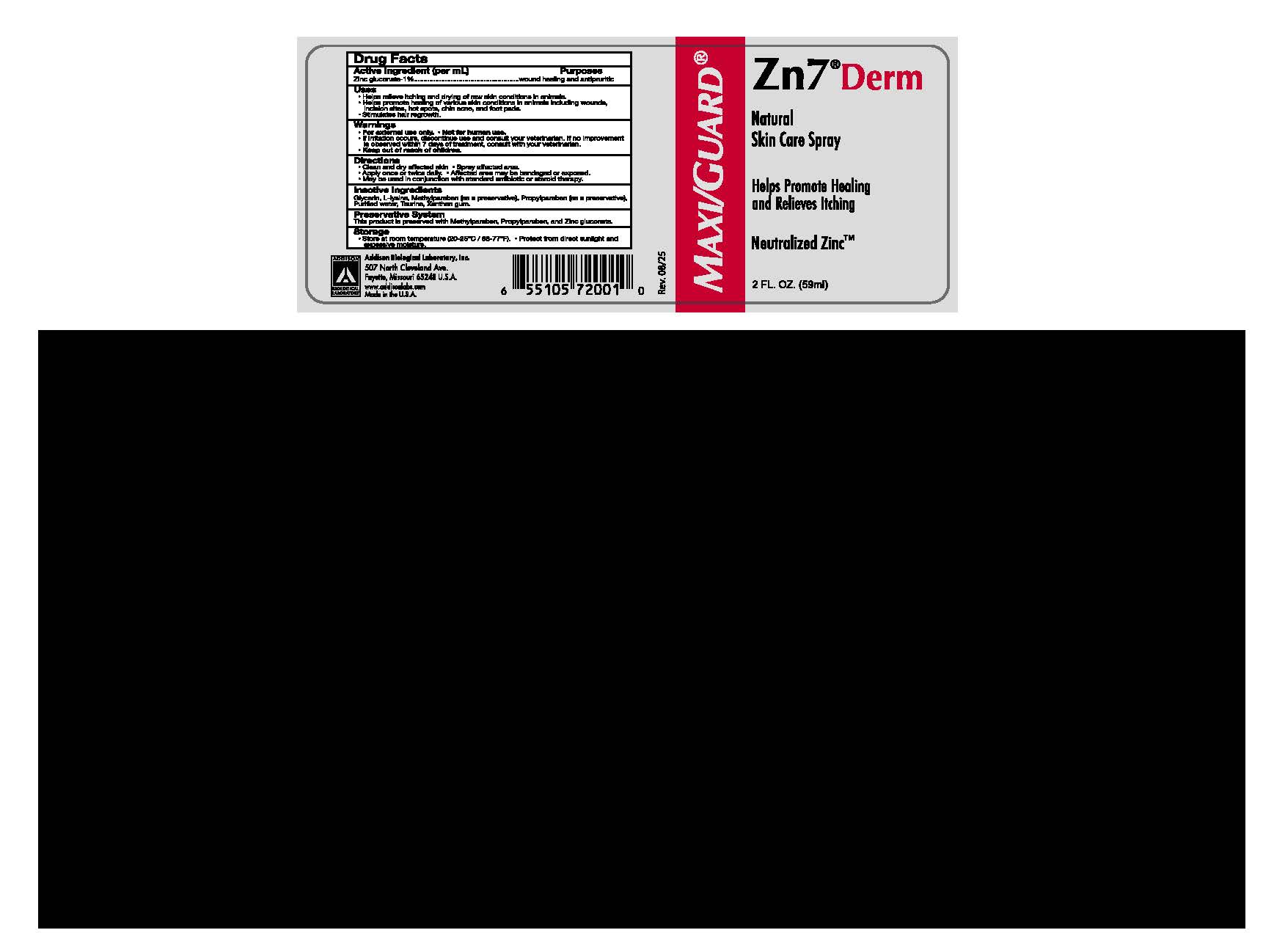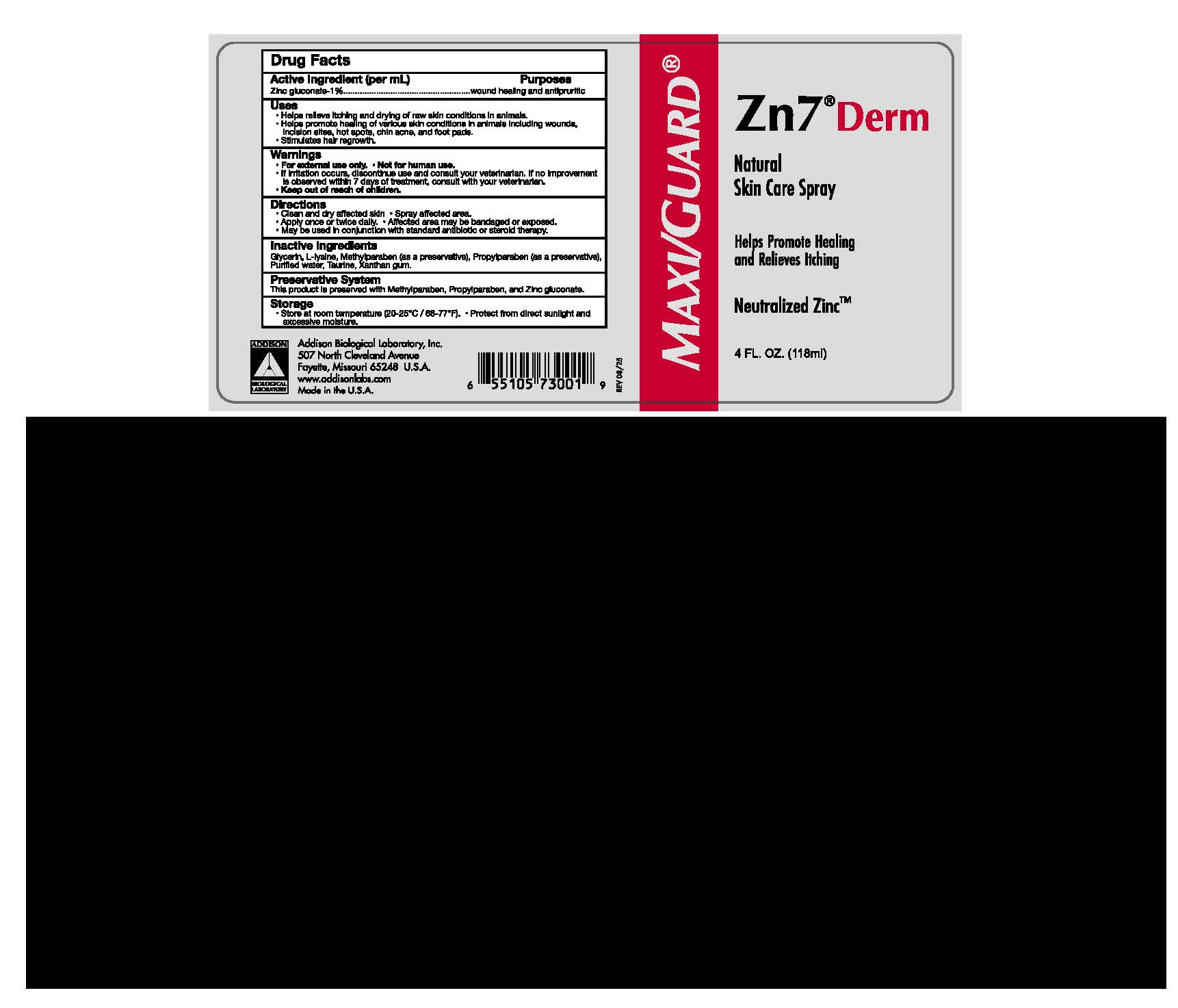 DRUG LABEL: Zn7 Derm
NDC: 86045-7100 | Form: SPRAY
Manufacturer: Addison Biological Laboratory, Inc.
Category: animal | Type: OTC ANIMAL DRUG LABEL
Date: 20251212

ACTIVE INGREDIENTS: ZINC GLUCONATE .011 g/1 mL
INACTIVE INGREDIENTS: WATER; TAURINE; METHYLPARABEN; PROPYLPARABEN; LYSINE; GLYCERIN; XANTHAN GUM

Zn7®Derm

INDICATIONS AND USAGE

INDICATIONS: A protective topical aid in the management of various pet skin conditions. Zn7 Derm is a natural neutralized zinc topical that provides relief from itching and drying of raw skin conditions. Can be used in conjunction with standard antibiotic or steroid therapy.

INSTRUCTIONS FOR USE

DIRECTIONS: Thoroughly clean and dry affected skin, then spray site. Apply once or twice daily. Affected areas may be bandaged or exposed. Please consult your veterinarian for additional advice or clinical evaluation.

INGREDIENTS: Purified Water, Glycerin, Zinc Gluconate, L-Lysine, Taurine, Xanthan Gum, Methylparaben, Propylparaben.

PRECAUTIONS

PRECAUTIONS: If no improvement is observed within 7 days of treatment, consult your veterinarian.

Keep out of reach of children.

Addison Biological Laboratory, Inc.

507 North Cleveland Avenue

Fayette, Missouri 65248 U.S.A

www.addisonlabs.com

Made in the U.S.A.

Rev. 08/25

PACKAGE LABEL

MAXI/GUARD®
Zn7®Derm

Natural
Skin Care Spray
For Veterinary
Helps Promote Healing
and Relieves Itching
Use Only

Neutralized Zinc™
1 FL. OZ. (29.5ml)

Drug Facts

Active Ingredient (per mL) PurposesZinc gluconate-1%___________________wound healing and antipruritic

Uses

- Helps relieve itching and drying of raw skin conditions in animals.
- Helps promote healing of various skin conditions in animals including wounds, incision sites, hot spots, chin acne, and foot pads.
- Stimulates hair regrowth.

Warnings

- For external use only.Not for human use.
- If irritation occurs, discontinue use ans consult your veterinarian.If no improvement is observer within 7 days of treatment, consult with your veterinarian.
- Keep out of reach of children.

Directions

- Clean and dry affected skin.Spray affected area.
- Apply once or twicw daily.Affected area may be bandaged or exposed.
- May be used in conjunction with standard antibiotic or steroid therapy.

Inactive Ingredients

Glycerin, L-lysine, Methylparaben (as a preservative), Propylparaben (as a preservative), Purified water, Taurine, Xanthan gum.

Preservative System

This product is preserved with Methylparaben, Propylparaben, and Zinc gluconate.

Storage

- Store at room temperature (20-25oC / 69-77oF). Protect from direct sunlight and excessive moisture.

Addison Biological Laboratory, Inc.
507 North Cleveland Avenue
Fayette, Missouri 65248 U.S.A
www.addisonlabs.com
Made in the U.S.A.

Rev. 08/25

PACKAGE LABEL

MAXI/GUARD®
Zn7®Derm

Natural
Skin Care Spray
For Veterinary
Helps Promote Healing
and Relieves Itching
Use Only

Neutralized Zinc™
2 FL. OZ. (59ml)

Drug Facts

Active Ingredient (per mL) Purposes
Zinc gluconate-1%___________________wound healing and antipruritic

Uses

- Helps relieve itching and drying of raw skin conditions in animals.
- Helps promote healing of various skin conditions in animals including wounds, incision sites, hot spots, chin acne, and foot pads.
- Stimulates hair regrowth.

Warnings

- For external use only.Not for human use.
- If irritation occurs, discontinue use ans consult your veterinarian.If no improvement is observer within 7 days of treatment, consult with your veterinarian.
- Keep out of reach of children.

Directions

- Clean and dry affected skin.Spray affected area.
- Apply once or twicw daily.Affected area may be bandaged or exposed.
- May be used in conjunction with standard antibiotic or steroid therapy.

Inactive Ingredients
Glycerin, L-lysine, Methylparaben (as a preservative), Propylparaben (as a preservative), Purified water, Taurine, Xanthan gum.

Preservative System
This product is preserved with Methylparaben, Propylparaben, and Zinc gluconate.

Storage
Store at room temperature (20-25oC / 69-77oF). Protect from direct sunlight and excessive moisture

Addison Biological Laboratory, Inc.
507 North Cleveland Avenue
Fayette, Missouri 65248 U.S.A
www.addisonlabs.com
Made in the U.S.A.

Rev. 08/25

PACKAGE LABEL

MAXI/GUARD®
Zn7®Derm

Natural
Skin Care Spray
For Veterinary
Helps Promote Healing
and Relieves Itching
Use Only

Neutralized Zinc™
4 FL. OZ. (118ml)

Drug Facts

Active Ingredient (per mL) Purposes
Zinc gluconate-1%___________________wound healing and antipruritic

Uses

- Helps relieve itching and drying of raw skin conditions in animals.
- Helps promote healing of various skin conditions in animals including wounds, incision sites, hot spots, chin acne, and foot pads.
- Stimulates hair regrowth.

Warnings

- For external use only.Not for human use.
- If irritation occurs, discontinue use ans consult your veterinarian.If no improvement is observer within 7 days of treatment, consult with your veterinarian.
- Keep out of reach of children.

Directions

- Clean and dry affected skin.Spray affected area.
- Apply once or twicw daily.Affected area may be bandaged or exposed.
- May be used in conjunction with standard antibiotic or steroid therapy.

Inactive Ingredients
Glycerin, L-lysine, Methylparaben (as a preservative), Propylparaben (as a preservative), Purified water, Taurine, Xanthan gum.

Preservative System
This product is preserved with Methylparaben, Propylparaben, and Zinc gluconate.

Storage
Store at room temperature (20-25oC / 69-77oF). Protect from direct sunlight and excessive moisture

Addison Biological Laboratory, Inc.
507 North Cleveland Avenue
Fayette, Missouri 65248 U.S.A
www.addisonlabs.com
Made in the U.S.A.

Rev. 08/25